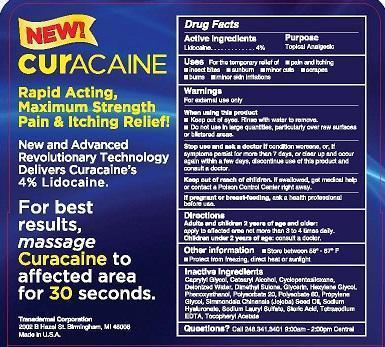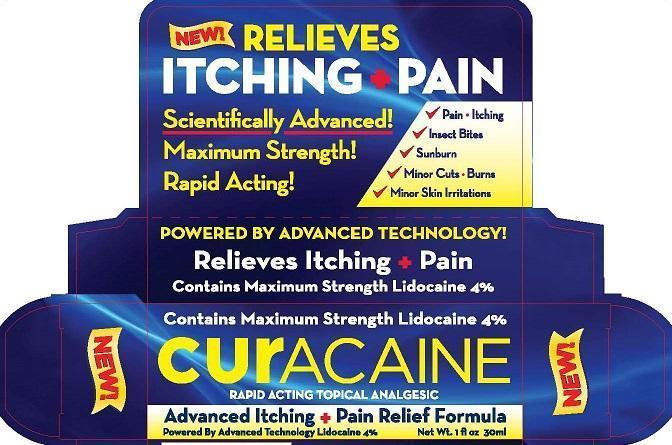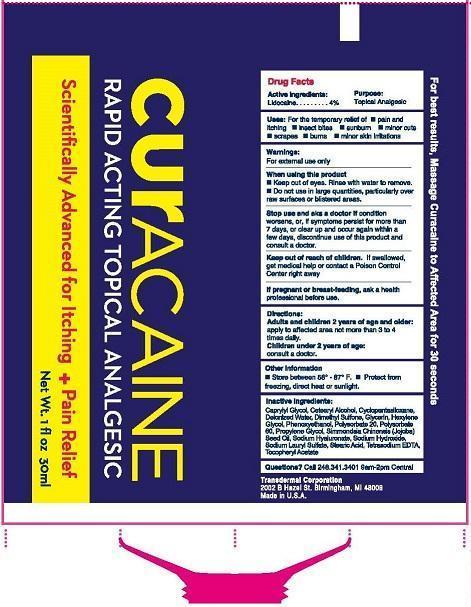 DRUG LABEL: CURACAINE
NDC: 51350-011 | Form: CREAM
Manufacturer: Transdermal Corp
Category: otc | Type: HUMAN OTC DRUG LABEL
Date: 20150415

ACTIVE INGREDIENTS: LIDOCAINE 4 g/100 mL
INACTIVE INGREDIENTS: CAPRYLYL GLYCOL; CETOSTEARYL ALCOHOL; CYCLOMETHICONE 5; WATER; DIMETHYL SULFONE; GLYCERIN; HEXYLENE GLYCOL; PHENOXYETHANOL; POLYSORBATE 20; POLYSORBATE 60; PROPYLENE GLYCOL; JOJOBA OIL; HYALURONATE SODIUM; SODIUM LAURYL SULFATE; STEARIC ACID; EDETATE SODIUM; .ALPHA.-TOCOPHEROL ACETATE

Active Ingredients

Lidocaine 4%

PURPOSE:

topical analgesic

Keep out of reach of children. If swallowed, get medical help or contact a Poison Control Center right away.

INDICATIONS AND USAGE

Uses for the temporary relief of

- pain and itching
- insect bites
- sunburn
- minor cuts
- scrapes
- burns
- minor skin irritations

Warnings

For external use only

When using this product

- Keep out of eyes. Rinse with water to remove.
- Do not use in large quantities, particularly over raw surfaces or blistered areas.
- If pregnant or breast feeding, ask a health professional before use.

Directions

Adults and children 2 years of age and older:

Apply to affected area not more than 3 to 4 times daily.

Children under 2 years of age: consult a doctor.

Inactive Ingredients

Caprylyl Glycol, Cetearyl Alcohol, Clyclopentasiloxane, Deionized water, Dimethyl Sulone, Glycerin, Hexylene Glycol, Phenoxyethanol, Polysorbate 20, Polysorbate 60, Propylene Glycol, Simmondsia Chinensis (Jojoba) Seed Oil, Sodium hyaluronate, Sodium Lauryl Sulfate, Stearic Acid, Tetrasodium EDTA, Tocopheryl Acetate

Stop use and ask a doctor if conditions worsens, or, if symptoms persist for more than 7 days, or clear up and occur again within a few days, discontinue use of the product and consult a doctor.